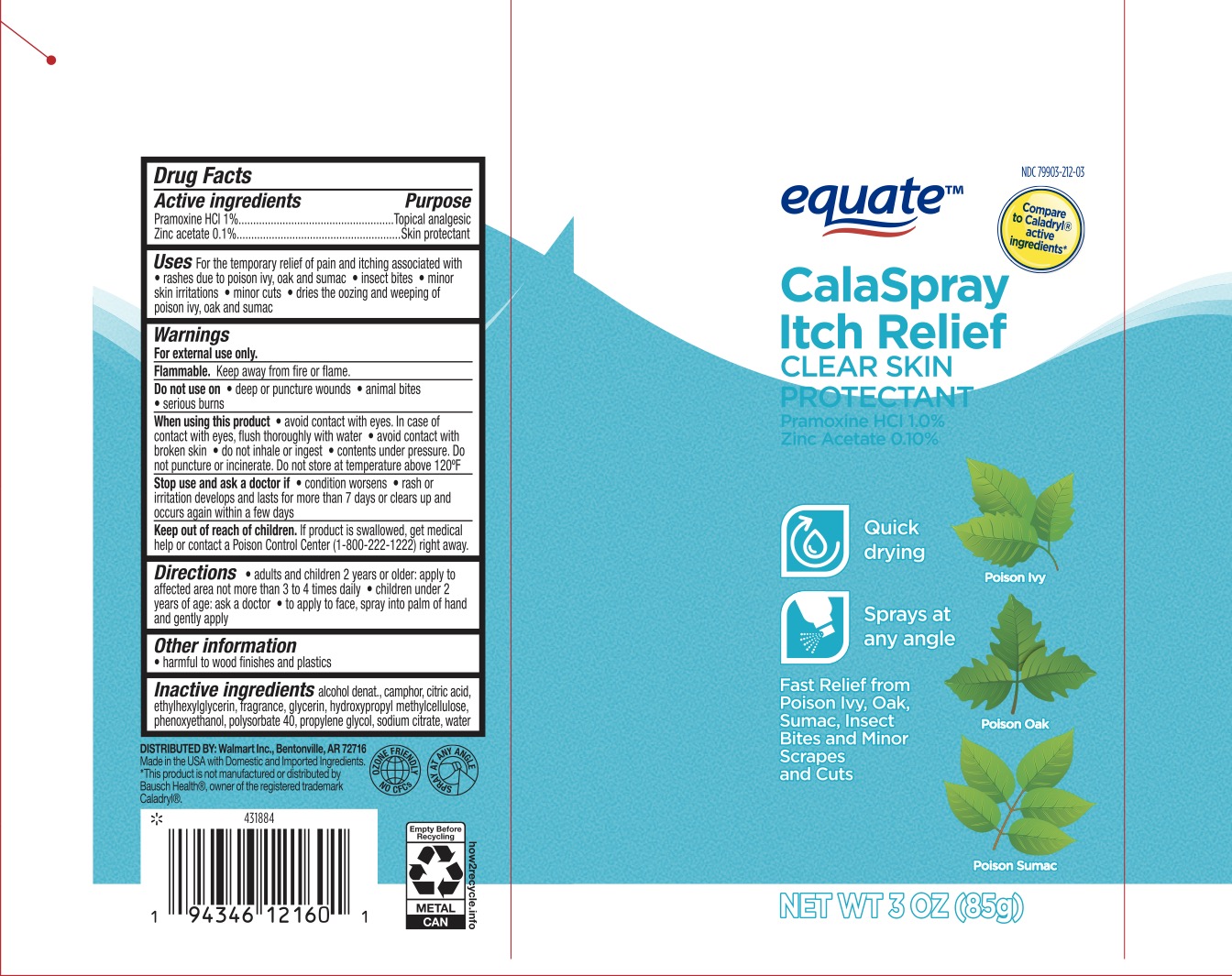 DRUG LABEL: Equate Calaspray
NDC: 79903-212 | Form: SPRAY
Manufacturer: Walmart Inc
Category: otc | Type: HUMAN OTC DRUG LABEL
Date: 20231226

ACTIVE INGREDIENTS: PRAMOXINE HYDROCHLORIDE 1 g/100 g; ZINC ACETATE 0.1 g/100 g
INACTIVE INGREDIENTS: PHENOXYETHANOL; WATER; HYPROMELLOSE, UNSPECIFIED; CITRIC ACID MONOHYDRATE; CAMPHOR (SYNTHETIC); ETHYLHEXYLGLYCERIN; PROPYLENE GLYCOL; SODIUM CITRATE; ALCOHOL; POLYSORBATE 40

Walmart Calaspray

ACTIVE INGREDIENT

Pramoxine HCl 1%, Zinc acetate 0.1%

PURPOSE

Topical analgesic / Skin protectant

INDICATIONS AND USAGE

For the temporary relief of pain and itching associated with

- rashes due to poison ivy, oak and sumac
- insect bites
- minor skin irritations
- minor cuts
- dries the oozing and weeping of poison ivy, oak, and sumac

WARNINGS

For external use only.

Flammable. Keep away from fire or flame.

Do not use on deep or puncture wounds, animal bites, or serious burns.

When using this product

- avoid contact with eyes. In case of contact with eyes, flush thoroughly with water.
- avoid contact with broken skin,
- do not inhale or ingest,
- contents under pressure. Do not puncture or incinerate. Do not store at temperature above 120F.

Stop use and ask a doctor if condition worsens, rash or irritation develops and lasts for more than 7 days or clears up and occurs again within a few days.

KEEP OUT OF REACH OF CHILDREN

If product is swallowed, get medical help or contact a Poison Control Center (1-800-222-1222) right away.

DOSAGE AND ADMINISTRATION

Adults and children 2 years or older: apply to affected are not more than 3 to 4 times daily. Children under 2 years of age: ask a doctor. To apply to face, spray into palm of hand and gently apply.

INACTIVE INGREDIENT

Alcohol denat., camphor, citric acid, ethylhexylglycerin, fragrance, glycerin, hydroxypropyl methylcellulose, phenoxyethanol, polysorbate 40, propylene glycol, sodium citrate, water.